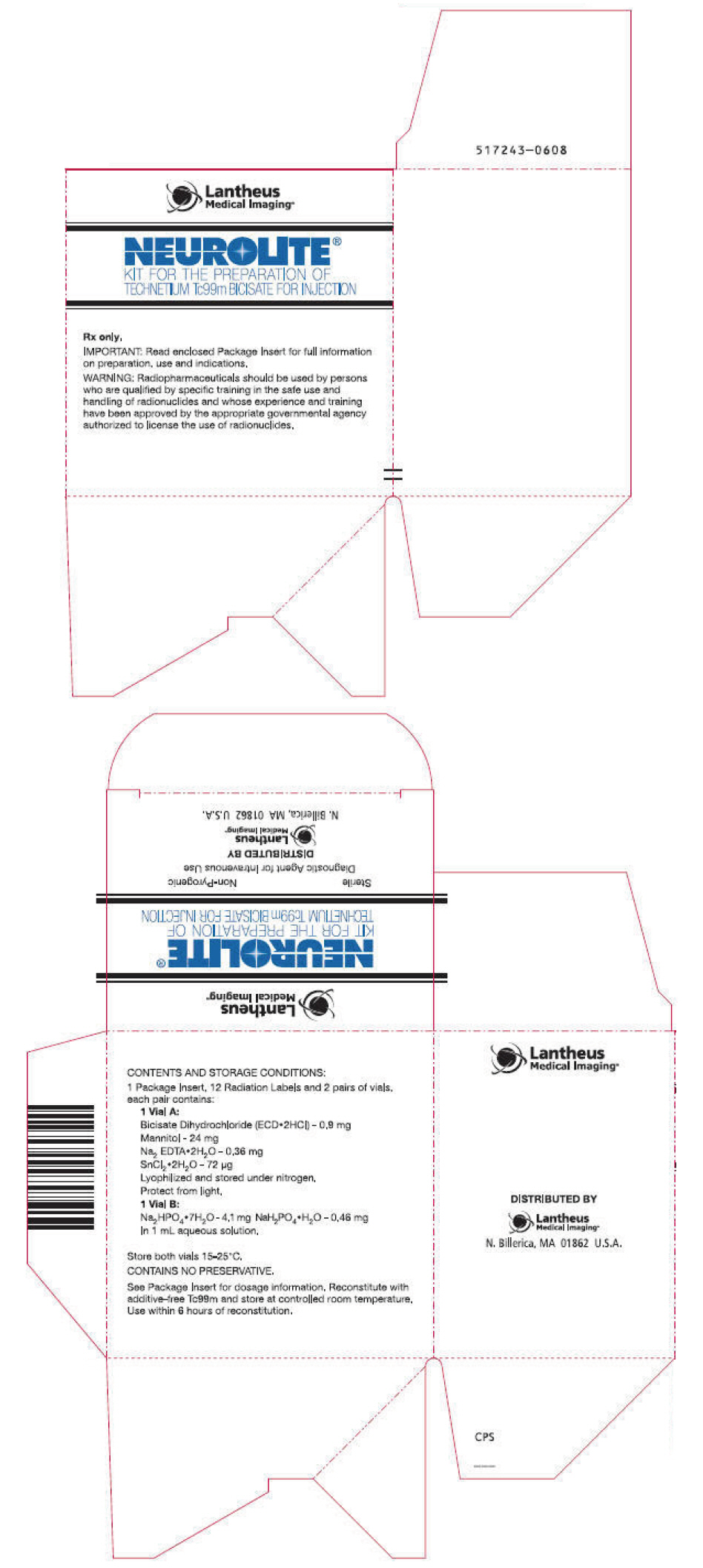 DRUG LABEL: NEUROLITE
NDC: 11994-006 | Form: KIT | Route: INTRAVENOUS
Manufacturer: Lantheus Medical Imaging, Inc.
Category: prescription | Type: HUMAN PRESCRIPTION DRUG LABEL
Date: 20221118

ACTIVE INGREDIENTS: BICISATE DIHYDROCHLORIDE 0.9 mg/1 1
INACTIVE INGREDIENTS: EDETATE DISODIUM 0.36 mg/1 1; MANNITOL 24 mg/1 1; STANNOUS CHLORIDE; SODIUM PHOSPHATE, DIBASIC, HEPTAHYDRATE 4.1 mg/1 mL; SODIUM PHOSPHATE, MONOBASIC, MONOHYDRATE 0.46 mg/1 mL; WATER

NEUROLITE®
Kit for the Preparation of Technetium Tc99m Bicisate for Injection
FOR DIAGNOSTIC USE

DESCRIPTION

This kit formulation consists of two nonradioactive vials: Vial A contains bicisate dihydrochloride (N, N'-1,2-ethylenediylbis-L-cysteine diethyl ester dihydrochloride) and a reducing agent as a lyophilized solid and vial B contains a buffer solution. Both vials are sterile and non-pyrogenic.

Vial A –
Bicisate dihydrochloride (ECD•2HCl) | 0.9 mg
Edetate disodium, dihydrate | 0.36 mg
Mannitol | 24 mg
Stannous chloride, dihydrate, theoretical
(SnCl2•2H2O) | 72 µg
Stannous chloride, dihydrate,
minimum (SnCl2•2H2O) | 12 µg
Total Tin, (stannous and stannic), dihydrate
(as SnCl2•2H2O) | 83 µg

The contents of vial A are lyophilized and stored under nitrogen. The pH of the solution before lyophilization is 2.7 ± 0.25. This vial is stored at 15-25°C. Protect from light.

Vial B –
Sodium phosphate dibasic heptahydrate |  | 4.1 mg
Sodium phosphate monobasic monohydrate |  | 0.46 mg
Water for Injection | qs | 1 mL

The contents of vial B are stored under air. The pH of the solution is 7.6 ± 0.4. This vial is stored at 15-25°C.

This drug is administered by intravenous injection for diagnostic use after reconstitution with sterile, non-pyrogenic, oxidant-free Sodium Pertechnetate Tc99m Injection. The precise structure of the Technetium complex is [N, N'-ethylenedi-L-cysteinato(3-)]oxo[99mTc] technetium (V), diethyl ester.

PHYSICAL CHARACTERISTICS

Technetium Tc99m decays by isomeric transition with a physical half-life of 6.02 hrs^1. Photons useful for the detection and imaging studies are listed in Table 1.

Table 1. Principle Radiation Emission Data
Radiation | Mean % / Disintegration | Mean Energy (KeV)
Gamma-2 | 89.07 | 140.5
^1Kocher, David C., "Radioactive Decay Data Tables", DOE/TIC 11026, 108 (1981).

External Radiation

The specific gamma ray constant for Tc99m is 5.4 microcoulombs/kg-MBq-hr (0.78R/mCi-hr) at 1cm. The first half value layer is 0.017cm of lead (Pb). Relative attenuation of the radiation emitted by this radionuclide results from the interposition of various thicknesses of Pb. The corresponding attenuation is shown in Table 2. To facilitate control of the radiation exposure from MBq (mCi) amounts of this radionuclide, a 0.25 cm thickness of Pb will attenuate the radiation by a factor of 1,000.

Table 2. Radiation Attenuation by Lead Shielding
Shield Thickness (Pb) cm | Coefficient of Attenuation
0.017 | 0.5
0.08 | 10^-1
0.16 | 10^-2
0.25 | 10^-3
0.33 | 10^-4

To correct for the physical decay of this radionuclide, the fractions that remain at selected time intervals after the time of calibration are shown in Table 3.

Table 3. Physical Decay Chart; Technetium Tc99m Half-Life 6.02 Hours
Hours | Fraction Remaining | Hours | Fraction Remaining
0* | 1.000 | 7 | .447
1 | .891 | 8 | .398
2 | .794 | 9 | .355
3 | .708 | 10 | .316
4 | .631 | 11 | .282
5 | .562 | 12 | .251
6 | .501
*Calibration Time

CLINICAL PHARMACOLOGY

General

Neurolite®, Kit for the Preparation of Technetium Tc99m Bicisate for Injection forms a stable, lipophilic complex which can cross the blood brain barrier. Technetium Tc99m Bicisate crosses intact cell membranes and the intact blood brain barrier by passive diffusion. Five percent of the injected dose remains in the blood at one hour. The amount of Technetium Tc99m Bicisate in the brain is stable until about 6 hours. After background clearance, images of the brain can be obtained from 10 minutes to 6 hours after injection. Optimal images occur 30-60 minutes after injection. Technetium Tc99m Bicisate is cleared primarily by the kidneys.

Pharmacokinetics

In a study in 16 normals (13 men and 3 women, mean age of 31 ± 10 years; mean weight of 72 ± 11 kg), the pharmacokinetic profile in blood best fits a three compartment model with half-lives of 43 seconds, 49.5 minutes and 533 minutes. The highest concentration of radioactivity measured in blood was found at 0.5 minutes after intravenous injection and was 13.9% of the injected dose. Technetium Tc99m Bicisate and its major metabolites are not protein-bound.

Metabolism

Technetium Tc99m Bicisate is metabolized by endogenous enzymes to the mono- and di-acids of Technetium Tc99m Bicisate that can be detected in blood and urine. No studies have been performed to compare the concentration of Technetium Tc99m Bicisate or its metabolites in normal, ischemic and infarcted cells.

Technetium Tc99m Bicisate is excreted primarily through the kidneys. Within two hours, 50% of the injected dose is excreted and by 24 hours, 74% is found in urine. It is not known whether the parent drug molecule or its metabolites are dialyzable. Fecal excretion accounts for 12.5% of the injected dose after 48 hours.

Pharmacodynamics

Localization of the parent compound in the brain in part depends upon both perfusion of the region and uptake of Technetium Tc99m Bicisate by the cell. Once in the brain cells, the parent compound is metabolized to polar, less diffusible compounds. Studies in 21 normal volunteers show cellular uptake of 4.8-6.5% of the injected dose at five minutes after injection. The degree of cell function or viability needed for uptake is not known. The degree of cell function or viability needed for metabolism of the parent compound to the less diffusible compounds has not been determined. The likelihood that the metabolic pathway is damaged by ischemia is not known. Whether or not and to what extent uptake correlates with viability or function is not known.

The pharmacodynamics of Neurolite have not been evaluated for differences associated with age, gender, weight and liver or renal impairment. It is not known whether dosage adjustments for these factors are needed.

Clinical Trials

Two clinical trials were performed in a total of 359 subjects (273 with stroke, 86 normal). Of these 56% were men and 44% were women. The mean age was 60.2 years (range 23 to 92 years). Subjects were 87.2% Caucasian, 8.4% Black, 2.2% Hispanic, 1.7% Oriental and 0.6% other.

Eligible patients had a confirmed stroke. Patients with other brain lesions were not evaluated. Subjects received Neurolite (mean dose range 10-30mCi) and underwent SPECT imaging and either CT or MRI scans within 0-30 days of the onset of signs and symptoms of stroke. CT or MRI and the administration of Neurolite occurred at different and variable times after the onset of a stroke. The effect of the timing on the accuracy of the images cannot be evaluated. The Neurolite scan results were blindly compared to unblinded CT/MRI results, the short standardized neurologic examination (SSNE) and the final diagnosis (e.g., the overall combined clinical impression with CT/MRI and SSNE).

In these studies, at least one of three blinded readers made a diagnosis of stroke in 190 (85%) of the Neurolite SPECT studies and in 238 (88%) CT/MRI studies. The Neurolite and CT/MRI imaging results versus the SSNE and final diagnosis were comparable. Neurolite had 11 false positive and 34 false negatives. CT/MRI had 0 false positive and 31 false negatives. Both Neurolite and CT/MRI missed strokes (true positives) that were identified by the other modality. The majority of the false negatives in either modality were within 15 days of the clinical stroke.

The trials were not designed to determine when Neurolite or CT/MRI studies could become positive in relationship to the time of the stroke. The relevance of the Neurolite scan results to the prediction of neurologic function or brain cell viability is not known. Also, not known is the ability of the Neurolite findings to distinguish between a stroke and pre-existing CNS lesions. Neurolite should not be used for these purposes. (See Pharmacodynamics Section).

INDICATIONS

Neurolite single photon emission computerized tomography (SPECT) is indicated as an adjunct to conventional CT or MRI imaging in the localization of stroke in patients in whom stroke has already been diagnosed.

Neurolite is not indicated for assessment of functional viability of brain tissue. Also, Neurolite is not indicated for distinguishing between stroke and other brain lesions.

CONTRAINDICATIONS

None known.

WARNINGS

None known.

PRECAUTIONS

General

USE WITH CAUTION IN PATIENTS WITH RENAL OR HEPATIC IMPAIRMENT. TECHNETIUM Tc99m BICISATE IS ELIMINATED PRIMARILY BY RENAL EXCRETION. WHETHER TECHNETIUM Tc99m BICISATE IS DIALYZABLE IS NOT KNOWN. DOSE ADJUSTMENTS IN PATIENTS WITH RENAL OR HEPATIC IMPAIRMENT HAVE NOT BEEN STUDIED.

Patients should be encouraged to drink fluids and to void frequently during the 2-6 hours immediately after injection to minimize radiation dose to the bladder and other target organs.

Contents of the vials are intended only for use in the preparation of Technetium Tc99m Bicisate and are not to be administered directly to the patient without first undergoing the preparation procedure.

The contents of each vial are sterile and non-pyrogenic. To maintain sterility, aseptic technique must be used during all operations in the manipulations and administration of Neurolite.

Technetium Tc99m Bicisate should be used within six hours of the time of preparation.

As with any other radioactive material, appropriate shielding should be used to avoid unnecessary radiation exposure to the patient, occupational workers, and other people.

Radiopharmaceuticals should be used only by physicians who are qualified by specific training in the safe use and handling of radionuclides.

Carcinogenesis, Mutagenesis, Impairment of Fertility

Studies have not been conducted to evaluate carcinogenic potential or effects on fertility. When tested in vitro, Neurolite prepared with decayed generator eluate induced unscheduled DNA synthesis in rat hepatocytes and caused an increased frequency of sister chromatid exchanges in CHO cells; but, it did not induce chromosome aberrations in human lymphocytes or cause gene mutations in the Ames test or in a CHO/HGPRT test. Unreacted bicisate dihydrochloride increased the apparent rate of gene mutation of the TA 97a strain of S. typhimurium in the Ames test; but, it did not demonstrate clastogenic activity in an in vivo micronucleus assay in mice.

Pregnancy: Teratogenic Effects

Animal reproduction studies have not been conducted with Technetium Tc99m Bicisate. It is also not known whether Technetium Tc99m Bicisate can cause fetal harm when administered to a pregnant woman or can affect reproduction capacity. Therefore, Technetium Tc99m Bicisate should not be administered to a pregnant woman unless the potential benefit justifies the potential risk to the fetus.

Nursing Mothers

Technetium Tc99m Pertechnetate can be excreted in human milk. Therefore, formula should be substituted for breast milk until the technetium has cleared from the body of the nursing woman.

Pediatric Use

Safety and effectiveness in the pediatric population has not been established.

Geriatric Use

Of 808 patients in clinical studies of NEUROLITE®, 421 patients were 65 or older and 190 were 75 or older. Based on the evaluation of the frequency of adverse events and review of vital signs and laboratory data, no overall differences in safety were observed between these subjects and younger subjects. Although reported clinical experience has not identified differences in response between elderly and younger patients, greater sensitivity of some older individuals cannot be ruled out.

NEUROLITE® is known to be substantially excreted by the kidney, and the risk of toxic reactions to this drug may be greater in patients with impaired renal function. Because elderly patients are more likely to have decreased renal function, care should be taken in dose selection, and it may be useful to assess renal function prior to administration.

ADVERSE REACTIONS

In clinical trials, Neurolite has been administered to 1063 subjects (255 normals, 808 patients). Of these, 566 (53%) were men and 494 (47%) were women. The mean age was 58 years (range 17 to 92 years). In the 808 patients, who had experienced neurologic events, there were 11 (1.4%) deaths, none of which were clearly attributed to Neurolite.

A total of 60 subjects experienced adverse reactions; the adverse reaction rates were comparable in the <65 year, and the >65 year age groups.

The following adverse effects were observed in ≤ 1% of the subjects: headache, dizziness, seizure, agitation/anxiety, malaise/somnolence, parosmia, hallucinations, rash, nausea, syncope, cardiac failure, hypertension, angina, and apnea/cyanosis.

In clinical trials of 197 patients, there were inconsistent changes in the serum calcium and phosphate levels. The cause of the changes has not been identified and their frequency and magnitude have not been clearly characterized. None of the changes required medical intervention.

DOSAGE AND ADMINISTRATION

Before administration, a patient should be well hydrated. After administration, the patient should be encouraged to drink fluids liberally and to void frequently.

The recommended dose range for intravenous administration for a 70 kg patient is 370-1110 MBq (10-30mCi). Dose adjustments for age, weight, gender or renal or hepatic impairment have not been studied.

The dose for the patient should be measured by a suitable radioactivity calibration system immediately before administration to the patient. Radiochemical purity should be checked before administration to the patient.

Neurolite, like other parenteral drug products, should be inspected visually for particulate matter and discoloration prior to administration whenever solution and container permit. Preparations containing particulate matter or discoloration should not be administered. They should be disposed of in a safe manner, in compliance with all applicable regulations.

Prior to reconstitution, vial A and vial B are stored at 15-25°C. Protect vial A from light.

Store at controlled room temperature after preparation.

Aseptic techniques and effective shielding should be employed in withdrawing doses for administration to patients. Waterproof gloves and effective shielding should be worn when handling the product.

RADIATION DOSIMETRY

The radiation doses to organs and tissues of an average patient (70 kg) for Technetium Tc99m Bicisate injected intravenously for 370 MBq (10 mCi) are shown in Table 4 and for 1110 MBq (30 mCi) are shown in Table 5.

Table 4. Radiation Absorbed Doses From 370 MBq (10 mCi) of Technetium Tc99m Bicisate
 | Estimated Absorbed Radiation Dose
 | 2.0 Hr. Void |  | 4.8 Hr. Void
 | mGy/ | rads/ | mGy/ | rads/
 | 370 MBq | 10 mCi | 370 MBq | 10 mCi
Organ
Bone Surfaces | 1.26 | 0.13 | 1.41 | 0.14
Brain | 2.04 | 0.20 | 2.04 | 0.20
Gallbladder Wall | 9.25 | 0.91 | 9.25 | 0.92
Intestine Wall
(Lower Large) | 4.81 | 0.47 | 5.55 | 0.55
Intestine (Small) | 3.48 | 0.35 | 3.70 | 0.38
Intestine Wall
(Upper Large) | 5.92 | 0.61 | 6.29 | 0.63
Kidneys | 2.70 | 0.27 | 2.74 | 0.27
Liver | 1.96 | 0.20 | 2.00 | 0.20
Lungs | 0.74 | 0.08 | 0.74 | 0.08
Ovaries | 2.00 | 0.22 | 2.96 | 0.30
Red Marrow | 0.89 | 0.09 | 1.00 | 0.10
Testes | 0.81 | 0.08 | 1.33 | 0.13
Thyroid | 1.30 | 0.13 | 1.30 | 0.13
Urinary Bladder Wall | 11.10 | 1.10 | 27.01 | 2.70
Total Body | 0.89 | 0.09 | 1.07 | 0.11

Table 5. Radiation Absorbed Doses From 1110 MBq (30 mCi) of Technetium Tc99m Bicisate
 | Estimated Absorbed Radiation Dose
 | 2.0 Hr. Void |  | 4.8 Hr. Void
 | mGy/ | rads/ | mGy/ | rads/
 | 1110 MBq | 30 mCi | 1110 MBq | 30 mCi
Organ
Bone Surfaces | 3.77 | 0.39 | 4.22 | 0.42
Brain | 6.11 | 0.61 | 6.11 | 0.61
Gallbladder Wall | 27.75 | 2.73 | 27.75 | 2.76
Intestine Wall
(Lower Large) | 14.43 | 1.41 | 16.65 | 1.65
Intestine (Small) | 10.43 | 1.05 | 11.10 | 1.14
Intestine Wall
(Upper Large) | 17.76 | 1.83 | 18.87 | 1.89
Kidneys | 8.10 | 0.81 | 8.21 | 0.81
Liver | 5.88 | 0.60 | 5.99 | 0.60
Lungs | 2.22 | 0.23 | 2.22 | 0.23
Ovaries | 5.99 | 0.66 | 8.88 | 0.90
Red Marrow | 2.66 | 0.26 | 3.00 | 0.29
Testes | 2.44 | 0.24 | 4.00 | 0.39
Thyroid | 3.89 | 0.39 | 3.89 | 0.39
Urinary Bladder Wall | 33.33 | 3.33 | 81.03 | 8.10
Total Body | 2.66 | 0.27 | 3.22 | 0.33
Radiation dosimetry calculations performed by Radiation Internal Dose Information Center, Oak Ridge Institute for Science and Education, PO Box 117, Oak Ridge, TN 37831-0117 (865) 576-3448.

INSTRUCTIONS FOR PREPARATION OF TECHNETIUM Tc99m BICISATE

Preparation of the Technetium Tc99m Bicisate from the NEUROLITE®, Kit for the Preparation of Technetium Tc99m Bicisate Injection, is done by the following aseptic procedure:

1. Prior to adding the Sodium Pertechnetate Tc99m Injection to vial B (the liquid vial), write the estimated activity, date, and time of preparation in the space provided on the vial label. Then tear off a radiation symbol and attach it to the neck of the vial.
2. Waterproof gloves should be worn during the preparation procedure. Remove the plastic disc from both vials and swab the top of each vial closure with alcohol to disinfect the surface.
3. Place vial B in a suitable radiation shield appropriately labeled with date, time of preparation, volume and activity.
4. With a sterile shielded syringe, aseptically add 3.70 GBq (100 mCi) sterile, non-pyrogenic, oxidant-free Sodium Pertechnetate Tc99m Injection, in approximately 2.0 mL, to vial B. Without withdrawing the needle, remove an equal volume of air to maintain pressure within the vial.
5. With a sterile syringe, rapidly inject 3.0 mL of Sodium Chloride Injection (0.9%) into vial A (the lyophilized vial) to dissolve the contents. Without withdrawing the needle, remove an equal volume of air to maintain pressure within the vial. Shake the contents of the vial for a few seconds.
6. With another sterile syringe, immediately (within 30 seconds) withdraw 1.0 mL of vial A and inject it into vial B. Discard vial A immediately.
7. Swirl the contents of the vial B for a few seconds, and allow this mixture to stand for thirty (30) minutes at room temperature.
8. Examine the vial contents for particulates and discoloration prior to patient administration. If particulate matter and/or discoloration are seen, DO NOT USE.
9. Assay the reaction vial using a suitable radioactivity calibration system. Record the Technetium Tc99m concentration, total volume, assay time and date, expiration time and lot number on the vial shield label and affix the label to the shield.
10. Store the reaction vial containing the Technetium Tc99m Bicisate at controlled room temperature until use; at such time the product should be aseptically withdrawn. The vial contains no preservative.

Note: Adherence to the above product reconstitution instructions is recommended.

Product should be used within 6 hours of preparation.

DETERMINATION OF RADIOCHEMICAL PURITY

The preparation and quality control of the agent should follow the procedure shown below.

Materials for TLC Procedure

Bakerflex silica gel IB-F, 2.5 x 7.5cm, Baker #4463-02
Solvent system: Ethyl Acetate, HPLC grade
Dose calibrator or gamma counter for measuring radioactivity
Small chromatographic developing tank
Syringe and shielded vials, as needed

TLC Procedure

Establish the radiochemical purity (RCP) of the final solution by the thin layer chromatography (TLC) using Baker-Flex silica gel IB-F plates and a solvent system of ethyl acetate. The RCP should be ≥90%.

Procedure – Using fresh ethyl acetate pour enough solvent into the developing tank to a depth of 3 to 4 mm. Seal the tank with Parafilm and allow 15 to 30 minutes for solvent equilibration. It is important to pre-equilibrate and preserve the integrity of the headspace in the chromatographic tank, otherwise unreproducible TLC results are obtained.
Note: Ethyl acetate is a skin/mucous membrane irritant and should be handled in a hood whenever possible.

With a pencil, draw a faint line across the TLC plate at heights of two (2) cm, four and one half (4.5) cm and seven (7) cm from the bottom of the TLC plate. Place approximately 5 µL of the final solution at the center of the 2 cm mark. This can be accomplished by using a syringe fitted with a 25 or 27 gauge needle and allowing a drop to form while holding the syringe in a vertical position. The diameter of the spot should not be greater than 10mm. Allow the spot to dry for 5 to 10 minutes, no longer.

Place the plate in the pre-equilibrated TLC tank and develop to the 7.0 cm line (about 15 minutes). Remove the plate and dry in a ventilated area.

Quantification

Cut the TLC plate at the 4.5 cm mark with scissors. Count the activity on each plate using a dose calibrator or a gamma counter. The top portion contains the Technetium Tc99m Bicisate and the bottom portion contains all radioimpurities.

Calculate the radiochemical purity using the following equation:

% Technetium Tc99m Bicisate = At x 100
At + Ab

Where: At = activity of the top piece and Ab = activity of the bottom piece.

HOW SUPPLIED

Lantheus Medical Imaging, Inc. Neurolite® Kit for the Preparation of Technetium Tc99m Bicisate for Injection, is supplied in kits of two (2) vials of A and two (2) vials of B (NDC # 11994-006-02); and five (5) vials of A and five (5) vials of B (NDC 11994-006-05). Included in each kit are one (1) package insert and twelve (12) radiation labels.

Prior to reconstitution, vial A and vial B are stored 15-25°C. Protect vial A from light.

Store at controlled room temperature after preparation.

Use within 6 hours of preparation.

This reagent kit is approved for distribution to persons licensed pursuant to the Code of Massachusetts Regulations 105 CMR 120.500 for the uses listed in 105 CMR 120.547 or 120.552 or under equivalent regulations of the U.S. Nuclear Regulatory Commission, Agreement States or Licensing States.

Distributed By
Lantheus Medical Imaging
331 Treble Cove Road
N. Billerica, Massachusetts 01862
USA
For Ordering Tel: Toll Free 800-299-3431
All Other Business: 800-362-2668
(For Massachusetts and International, call 978-667-9531)
Printed in the U.S.A.

513073-0719
July 2019

PRINCIPAL DISPLAY PANEL - Kit Package

Lantheus
Medical Imaging®

NEUROLITE®
KIT FOR THE PREPARATION OF
TECHNETIUM Tc99m BICISATE FOR INJECTION

Rx only,
IMPORTANT: Read enclosed Package Insert for full information
on preparation, use and indications.
WARNING: Radiopharmaceuticals should be used by persons
who are qualified by specific training in the safe use and
handling of radionuclides and whose experience and training
have been approved by the appropriate governmental agency
authorized to license the use of radionuclides.